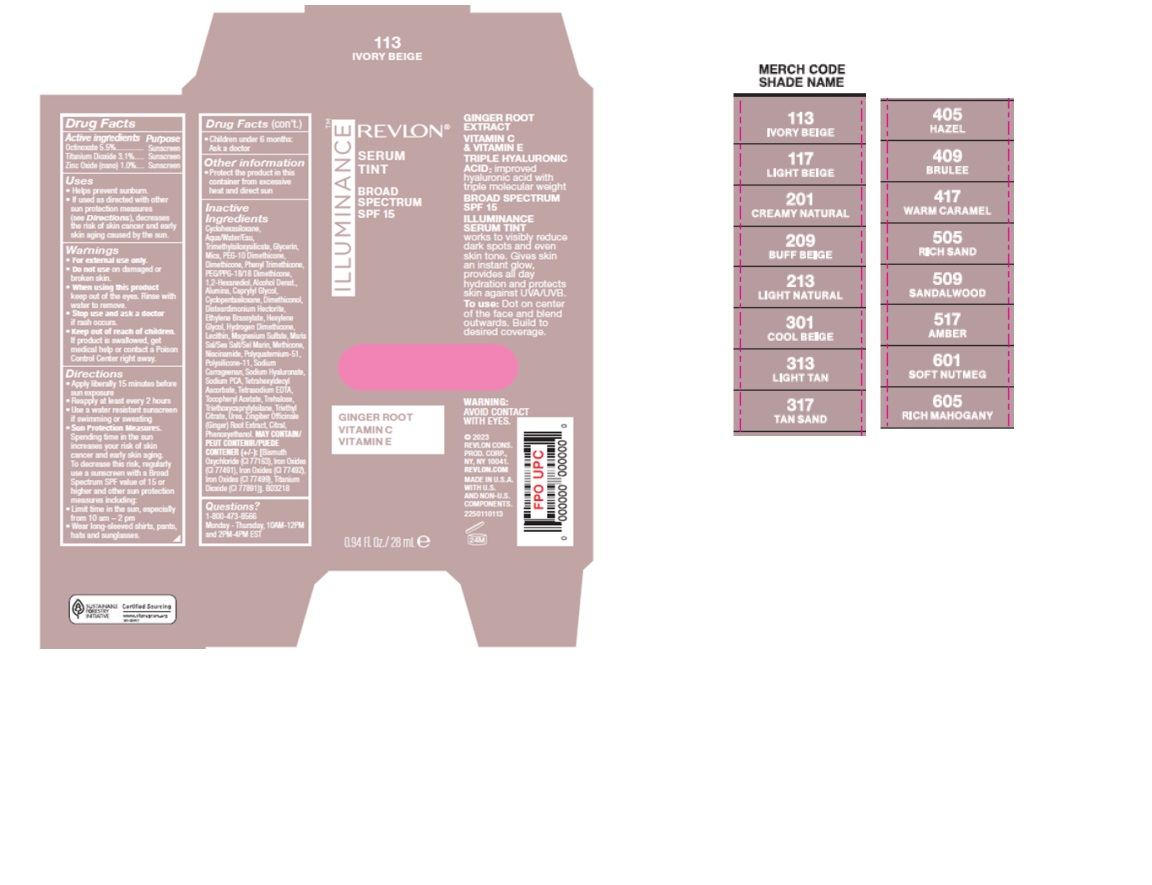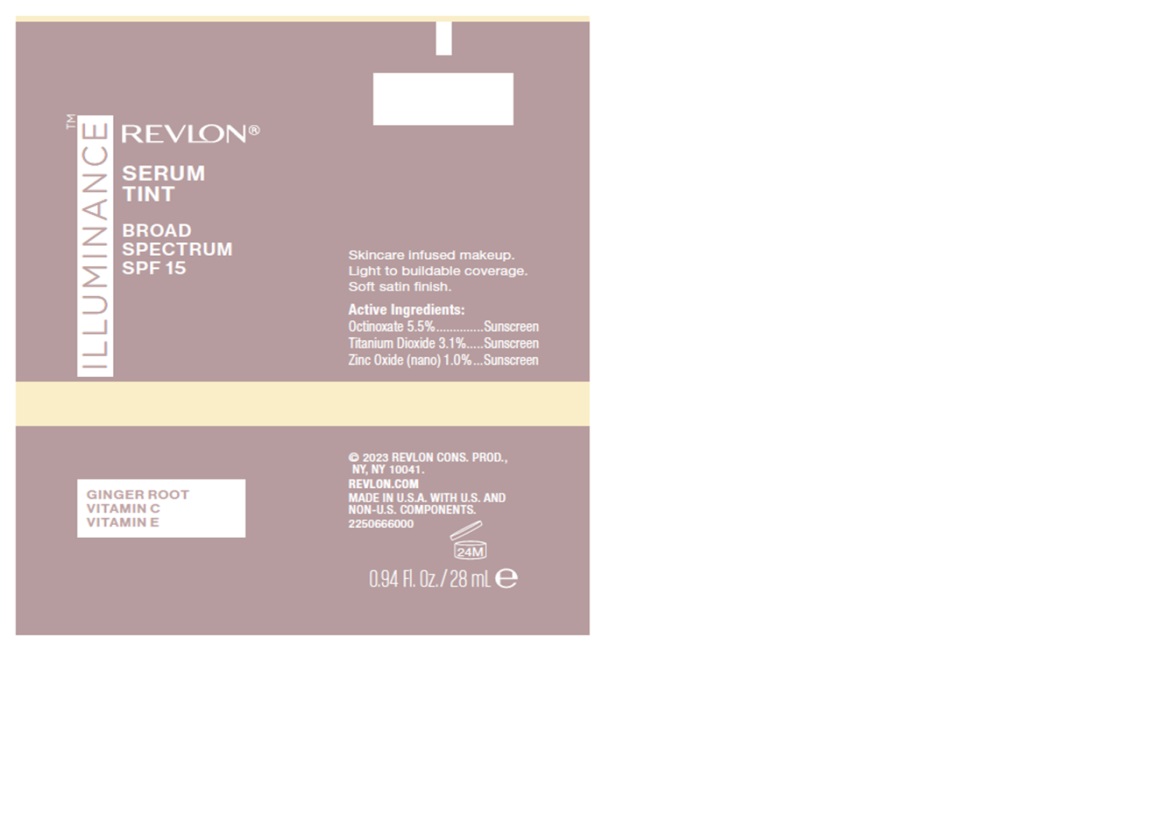 DRUG LABEL: RV Illuminance Serum Tint Broad Spectrum 15
NDC: 10967-696 | Form: CREAM
Manufacturer: REVLON CONSUMER PR Consumer Products Corp
Category: otc | Type: HUMAN OTC DRUG LABEL
Date: 20241224

ACTIVE INGREDIENTS: TITANIUM DIOXIDE 0.868 g/28 mL; ZINC OXIDE 0.28 g/28 mL; OCTINOXATE 1.54 g/28 mL
INACTIVE INGREDIENTS: TRIMETHYLSILOXYSILICATE (M/Q 0.6-0.8); GLYCERIN; MICA; CYCLOMETHICONE 6; DIMETHICONE; CYCLOMETHICONE 5; EDETATE SODIUM; .ALPHA.-TOCOPHEROL ACETATE; TREHALOSE; UREA; 1,2-HEXANEDIOL; ALUMINUM OXIDE; DISTEARDIMONIUM HECTORITE; LECITHIN, SOYBEAN; GINGER; CITRAL; FERRIC OXIDE RED; DIMETHICONOL (100000 CST); HEXYLENE GLYCOL; HYALURONATE SODIUM; TETRAHEXYLDECYL ASCORBATE; FERRIC OXIDE YELLOW; PHENOXYETHANOL; WATER; PEG/PPG-18/18 DIMETHICONE; ALCOHOL; PEG-10 DIMETHICONE (600 CST); CAPRYLYL GLYCOL; ETHYLENE BRASSYLATE; PHENYL TRIMETHICONE; HYDROGEN DIMETHICONE (13 CST); SEA SALT; POLYQUATERNIUM-51 (2-METHACRYLOYLOXYETHYL PHOSPHORYLCHOLINE/N-BUTYL METHACRYLATE; 3:7); TRIETHYL CITRATE; BISMUTH OXYCHLORIDE; FERROSOFERRIC OXIDE; MAGNESIUM SULFATE, UNSPECIFIED; METHICONE (20 CST); NIACINAMIDE; DIMETHICONE/VINYL DIMETHICONE CROSSPOLYMER (SOFT PARTICLE); CARRAGEENAN; SODIUM PYRROLIDONE CARBOXYLATE; TRIETHOXYCAPRYLYLSILANE

REVLON ILLUMINANCE SERUM TINT BROAD SPECTRUM 15 (Shade: Creamy Natural)

ACTIVE INGREDIENTS

Active Ingredients Purpose

Octinoxate 5.5% ...............Sunscreen

Titanium dioxide 3.1%...... Sunscreen

Zinc oxide (nano) 1.0 %.....Sunscreen

Uses

- Helps prevent sunburn.
- If used as directed with other sun protection measures (see Directions), decreases the risk of skin cancer and early skin aging caused by the sun.

Warnings

- For external use only.
- Do not use on damaged or broken skin.
- When using this product keep out of eyes. Rinse with water to remove.
- Stop use and ask a doctor if rash occurs.
- Keep out of reach of children. If swallowed, get medical help or contact a Poison Control Center right away.

Directions

- Apply liberally 15 minutes before sun exposure.
- Reapply at least every 2 hours.
- Use a water resistant sunscreen if swimming or sweating.
- Sun Protection Measures. Spending time in the sun increases your risk of skin cancer and early skin aging. To decrease this risk, regularly use a sunscreen with a Broad Spectrum SPF value of 15 or higher and other sun protection measures including:
- Limit time in the sun, especially from 10 a.m.–2 p.m.
- Wear long-sleeved shirts, pants, hats, and sunglasses
- Children under 6 months of age: Ask a doctor

Other information

Protect the product in this container from excessive heat and direct sun

Inactive ingredients

Inactive Ingredients: Cyclohexasiloxane, Aqua/Water/Eau, Trimethylsiloxysilicate, Glycerin, Mica, PEG-10 Dimethicone, Dimethicone, Phenyl Trimethicone, PEG/PPG-18/18 Dimethicone, 1,2-Hexanediol, Alcohol Denat., Alumina, Caprylyl Glycol, Cyclopentasiloxane, Dimethiconol, Disteardimonium Hectorite, Ethylene Brassylate, Hexylene Glycol, Hydrogen Dimethicone, Lecithin, Magnesium Sulfate, Maris Sal/Sea Salt/Sel Marin, Methicone, Niacinamide, Polyquaternium-51, Polysilicone-11, Sodium Carrageenan, Sodium Hyaluronate, Sodium PCA, Tetrahexyldecyl Ascorbate, Tetrasodium EDTA, Tocopheryl Acetate, Trehalose, Triethoxycaprylylsilane, Triethyl Citrate, Urea, Zingiber Officinale (Ginger) Root Extract, Citral, Phenoxyethanol.

MAY CONTAIN/PEUT CONTENIR/PUEDE CONTENER (+/-): [Bismuth Oxychloride (CI 77163), Iron Oxides (CI 77491), Iron Oxides (CI 77492), Iron Oxides (CI 77499), Titanium Dioxide (CI 77891).]. B03218

Questions?

1-800-473-8566

Monday - Thursday, 10AM - 12PM and 2PM - 4PM EST

RECENT MAJOR CHANGES

sections were updated to align with FDAs new section breakdown requirements

Keep out of reach of children

If product is swallowed, get medical help or contact a Poison Control Center right away.

Purpose

Sunscreen

Carton Packaging